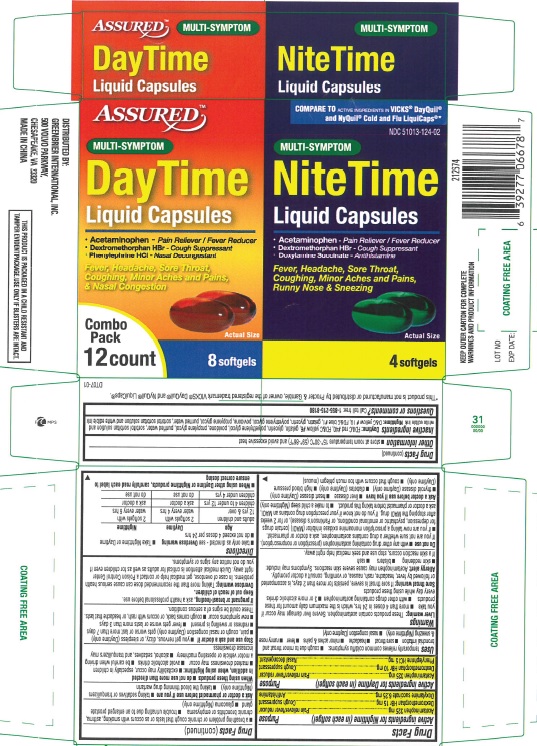 DRUG LABEL: DayTime and NiteTime
NDC: 51013-124 | Form: KIT | Route: ORAL
Manufacturer: PuraCap Pharmaceutical LLC
Category: otc | Type: HUMAN OTC DRUG LABEL
Date: 20191210

ACTIVE INGREDIENTS: ACETAMINOPHEN 325 mg/1 1; DEXTROMETHORPHAN HYDROBROMIDE 10 mg/1 1; PHENYLEPHRINE HYDROCHLORIDE 5 mg/1 1; ACETAMINOPHEN 325 mg/1 1; DEXTROMETHORPHAN HYDROBROMIDE 15 mg/1 1; DOXYLAMINE SUCCINATE 6.25 mg/1 1
INACTIVE INGREDIENTS: FD&C RED NO. 40; FD&C YELLOW NO. 6; GELATIN; GLYCERIN; POLYETHYLENE GLYCOL, UNSPECIFIED; POVIDONE; PROPYLENE GLYCOL; WATER; SORBITOL; D&C YELLOW NO. 10; FD&C BLUE NO. 1; GELATIN; GLYCERIN; POLYETHYLENE GLYCOL, UNSPECIFIED; POVIDONE; PROPYLENE GLYCOL; WATER; SORBITOL

DayTime and NiteTime Liquid Capsules

Active ingredients (in each softgel)

Active ingredients for DayTime (in each Softgel)

Acetaminophen 325 mg

Dextromethorphan HBr 10 mg

Phenylephrine HCl 5 mg

Active ingredients for NiteTime (in each Softgel)

Acetaminophen 325 mg

Dextromethorphan HBr 15 mg

Doxylamine succinate 6.25 mg

Purpose

DayTime Liquid Capsules

Pain reliever/fever reducer

Cough suppressant

Nasal decongestant

NiteTime Liquid Capsules

Pain reliever/fever reducer

Cough suppressant

Antihistamine

Uses

temporarily relieves common cold/flu symptoms:

- nasal congestion (DayTime only)
- cough due to minor throat and bronchial irritation
- sore throat
- headache
- minor aches and pains
- fever
- runny nose and sneezing (NiteTime only)

Warnings

Liver warning

These products contain acetaminophen. Severe liver damage may occur if you take:

- more than 4,000 mg of acetaminophen in 24 hours
- with other drugs containing acetaminophen
- 3 or more alcoholic drinks daily while using this product

Sore throat warning

If sore throat is severe, lasts for more than 2 days, occurs with or is followed by fever, headache, rash, nausea, or vomiting, see a doctor promptly.

Do not use

- with any other drug containing acetaminophen (prescription or nonprescription). If you are not sure whether a drug contains acetaminophen, ask a doctor or pharmacist.
- if you are now taking a prescription monoamine oxidase inhibitor (MAOI) (certain drugs for depression, psychiatric or emotional conditions, or Parkinson's disease), or for 2 weeks after stopping the MAOI drug. If you do not know if your prescription drug contains an MAOI, ask a doctor or pharmacist before taking this product.
- to make a child sleep (NiteTime only)

Ask a doctor before use if you have

- liver disease
- heart disease (DayTime only)
- thyroid disease (DayTime only)
- diabetes (DayTime only)
- high blood pressure (DayTime only)
- trouble urinating due to an enlarged prostate gland
- cough that occurs with excessive phlegm (mucus)
- persistent or chronic cough as occurs with smoking, asthma, or emphysema, and (for NiteTime only) chronic bronchitis
- glaucoma (NiteTime only)

Ask a doctor or pharmacist before use if you are

- taking the blood thinning drug warfarin
- taking sedatives or tranquilizers (NiteTime only)

When using this product, do not use more than directed.

In addition, when using NiteTime:

- excitability may occur, especially in children
- marked drowsiness may occur
- avoid alcoholic drinks
- be careful when driving a motor vehicle or operating machinery
- alcohol, sedatives, and tranquilizers may increase drowsiness

Stop use and ask a doctor if

- you get nervous, dizzy, or sleepless (DayTime only)
- pain, cough and (for DayTime only) nasal congestion gets worse or last more than 7 days
- redness or swelling is present
- fever gets worse or lasts more than 3 days
- redness or swelling is present
- new symptoms occur
- cough comes back or occurs with rash or headache that lasts.

These could be signs of a serious condition.

PREGNANCY OR BREAST FEEDING

If pregnant or breast-feeding, ask a health professional before use.

Keep out of reach of children.

Overdose warning

Taking more than the recommended dose can cause serious health problems. In case of overdose, get medical help or contact a Poison Control Center right away. Quick medical attention is critical for adults as well as for children even if you do not notice any signs or symptoms.

Directions

- Take only as directed - see Overdose warning
- swallow whole; do not crush, chew, or dissolve
- do not exceed 4 doses per 24 hours

Age | DayTime | NiteTime
adults and children 12 years of age and over | take 2 softgels with water every 4 hours | take 2 softgels with water every 6 hours
children 4 to under 12 years of age | ask a doctor | ask a doctor
children under 4 years of age | do not use | do not use

When using other DayTime or NiteTime products, carefully read each label to ensure correct dosing

Other information

- store at room temperature 15°-30°C (59°-86°F) and avoid excessive heat

Inactive ingredients

NiteTime: D&C yellow # 10, FD&C blue #1, gelatin, glycerin, polyethylene glycol, povidone, propylene glycol, purified water, sorbitol special and white edible ink

DayTime: FD&C red #40, FD&C yellow #6, gelatin, glycerin, polyethylene glycol, povidone, propylene glycol, purified water, sorbitol special and white edible ink

Questions or comments?

Call toll free: 1-855-215-8180

Principal Display Panel

ASSURED DayTime and NiteTime Liquid Capsules

Combo Pack 12 count

NDC 51013-124-02

*Compare to the active ingredients in VICKS® DayQuil® and NyQuil® Cold and Flu LiquiCaps®